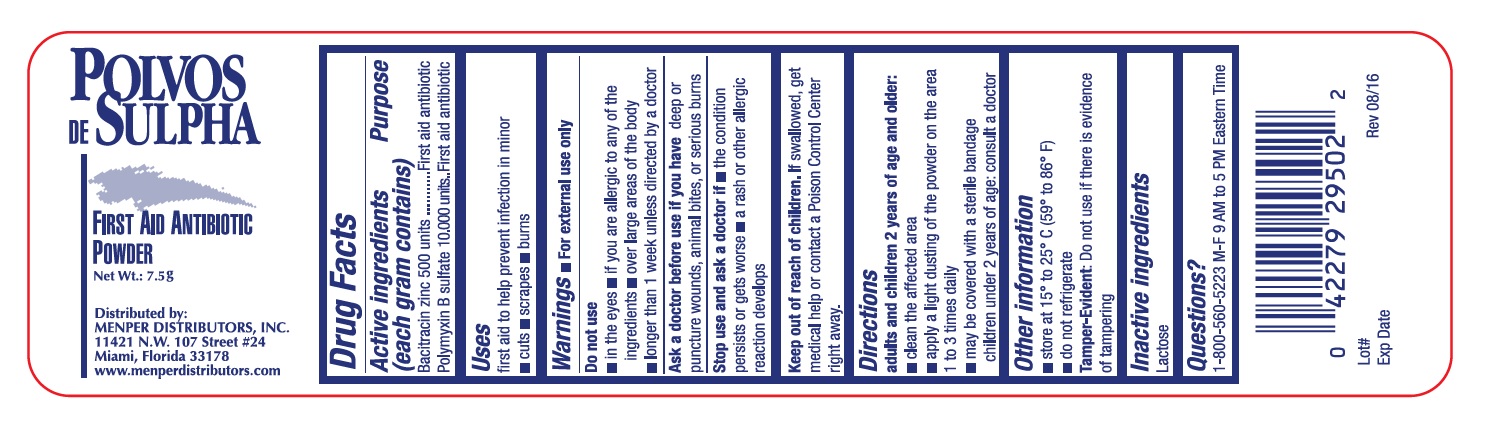 DRUG LABEL: Polvos de Sulpha
NDC: 53145-304 | Form: POWDER
Manufacturer: Menper Distributors Inc.
Category: otc | Type: HUMAN OTC DRUG LABEL
Date: 20250108

ACTIVE INGREDIENTS: BACITRACIN ZINC 500 [USP'U]/1 g; POLYMYXIN B SULFATE 10000 [USP'U]/1 g
INACTIVE INGREDIENTS: LACTOSE, UNSPECIFIED FORM

Polvos de Sulpha

Drug Facts

Active ingredients (each gram contains) Purpose

Bacitracin zinc 500 units.....................................................................................First aid

Polymyxin B sulfate 10,000 units.........................................................................First aid antibiotic

Purpose

First aid

First aid antibiotic

Uses

first aid to help prevent infection in minor

- cuts
- scrapes
- burns

WARNINGS

For fexternal use only

Ask a doctor before use if you have

deep or puncture wounds, animal bites, or serious burns

Stop use and ask a doctor if

The condition persists or gets worsen

a rash or other alergic reaction develops

Keep out of reach of childrens

If swallowed, get medical help or contact a Poison Control Center right away.

Directions Adults and children 2 years of age and older

- clean the affected area
- apply a light dusting of the powder on the area 1 to 3 times daily
- may be covered with a sterile bandages children under 2 years of age: consult a doctor

Other Information

- store at 15° to 25° C (59° to 86° F)
- do not refrigerate

Tamper-Evident: Do not use if there is evidence of tampering

Inactive ingredients

Lactose

Questions?

1-800-560-5223 M-F 9 AM to 5 PM Eastern Time